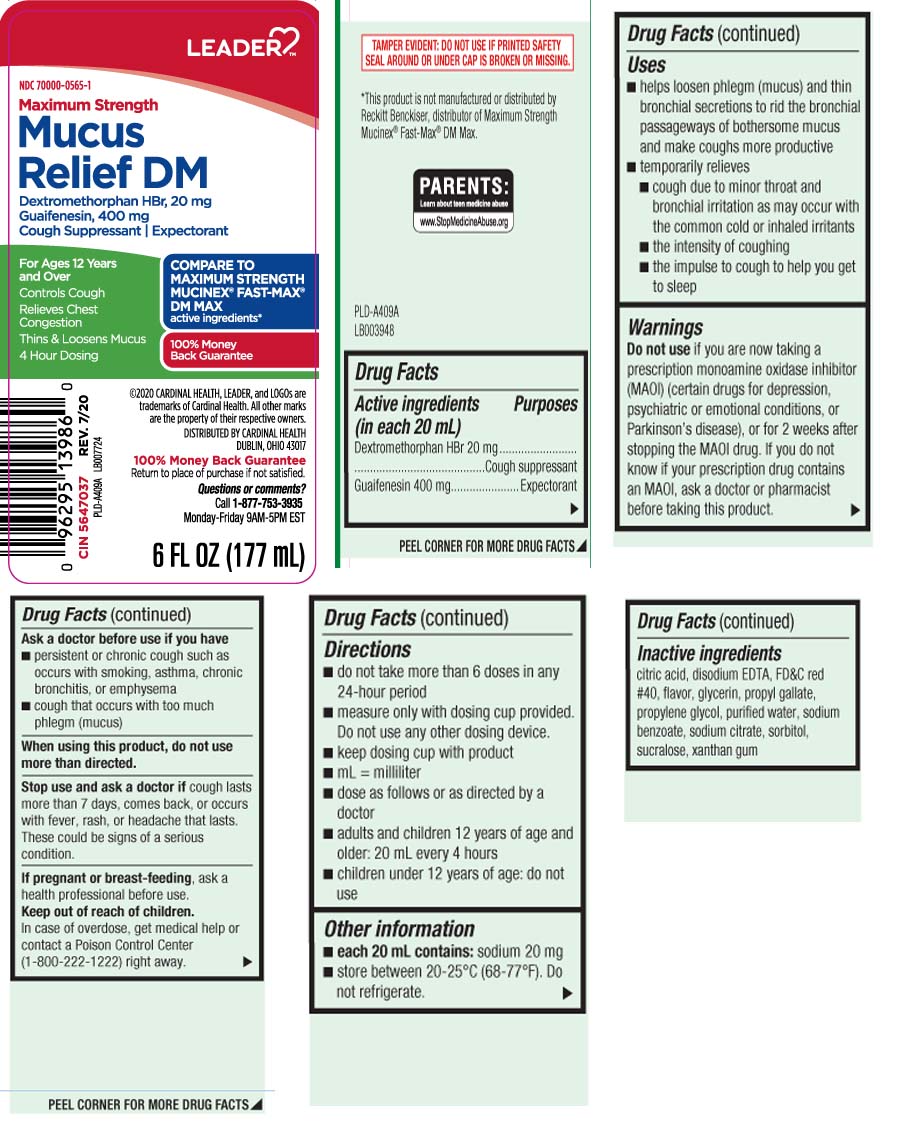 DRUG LABEL: Mucus Relief DM
NDC: 70000-0565 | Form: LIQUID
Manufacturer: Cardinal Health (Leader) 70000
Category: otc | Type: HUMAN OTC DRUG LABEL
Date: 20250722

ACTIVE INGREDIENTS: DEXTROMETHORPHAN HYDROBROMIDE 20 mg/20 mL; GUAIFENESIN 400 mg/20 mL
INACTIVE INGREDIENTS: ANHYDROUS CITRIC ACID; EDETATE CALCIUM DISODIUM; FD&C RED NO. 40; GLYCERIN; PROPYL GALLATE; PROPYLENE GLYCOL; WATER; SODIUM BENZOATE; SODIUM CITRATE; SORBITOL; SUCRALOSE; XANTHAN GUM

Drug Facts

Active ingredients (in each 20 mL)

Dextromethorphan HBr 20 mg

Guaifenesin 400 mg

Purposes

Cough suppressant

Expectorant

Uses

- helps loosen phlegm (mucus) and thin bronchial secretions to rid the bronchial passageways of botherosme mucus and make coughs more productive
- temporarily relieves
  - cough due to minor throat and bronchial irritation as may occur with the common cold or inhaled irritants
  - the intensity of coughing
  - the impulse to cough to help you get to sleep

Warnings

Do not use

if you are now taking a prescription monoamine oxidase inhibitor (MAOI) (certain drugs for depression, psychiatric or emotional conditions, or Parkinson's disease), or for 2 weeks after stopping the MAOI drug. If you do not know if your prescription drug contains an MAOI, ask a doctor or pharmacist before taking this product.

Ask a doctor before use if you have

- persistent or chronic cough such as occurs with smoking, asthma, chronic bronchitis, or emphysema
- cough that occurs with too much phlegm (mucus)

When using this product,

do not use more than directed.

Stop use and ask a doctor if

cough lasts more than 7 days, comes back, or occurs with fever, rash, or headache that lasts. These could be signs of a serious condition.

If pregnant or breast-feeding,

ask a health professional before use.

Keep out of reach of children.

In case of overdose, get medical help or contact a Poison Control Center (1-800-222-1222) right away.

Directions

- do not take more than 6 doses in any 24-hour period
- measure only with dosing cup provided. Do not use any other dosing device.
- keep dosing cup with product
- mL = milliliter
- dose as follows or as directed by a doctor
- adults and children 12 years of age and older: 20 mL every 4 hours
- children under 12 years of age: do not use

Other information

- each 20 mL contains: sodium 20 mg
- store between 20-25ºC (68-77ºF). Do not refrigerate.

Inactive ingredients

citric acid, disodium EDTA, FD&C red #40, flavor, glycerin, propyl gallate, propylene glycol, purified water, sodium benzoate, sodium citrate, sorbitol, sucralose, xanthan gum

Principal Display Panel

COMPARE TO MAXIMUM STRENGTH MUCINEX® FAST-MAX® DM MAX active ingredient

Maximum Strength Mucus Relief DM

Dextromethorphan HBr 20 mg

Guaifenesin 400 mg

Cough Suppressant | Expectorant

For Ages 12 Years and Over

Controls Cough

Relieves Chest Congestion

Thin & Loosens Mucus 4 Hour Dosing

Questions or comments? Call 1-877-753-3935 Monday-Friday 9AM-5PM EST

FL OZ (mL)

*This product is not manufactured or distributed by Reckitt Benckiser, distributor of Maximum Strength Mucinex® Fast-Max® DM Max.

TAMPER EVIDENT: DO NOT USE IF PRINTED SAFETY SEAL AROUND OR UNDER CAP IS BROKEN OR MISSING.

DISTRIBUTED BY CARDINAL HEALTH

DUBLIN, OHIO 43017

Package Label

LEADER Maximum Strength Mucus Relief DM